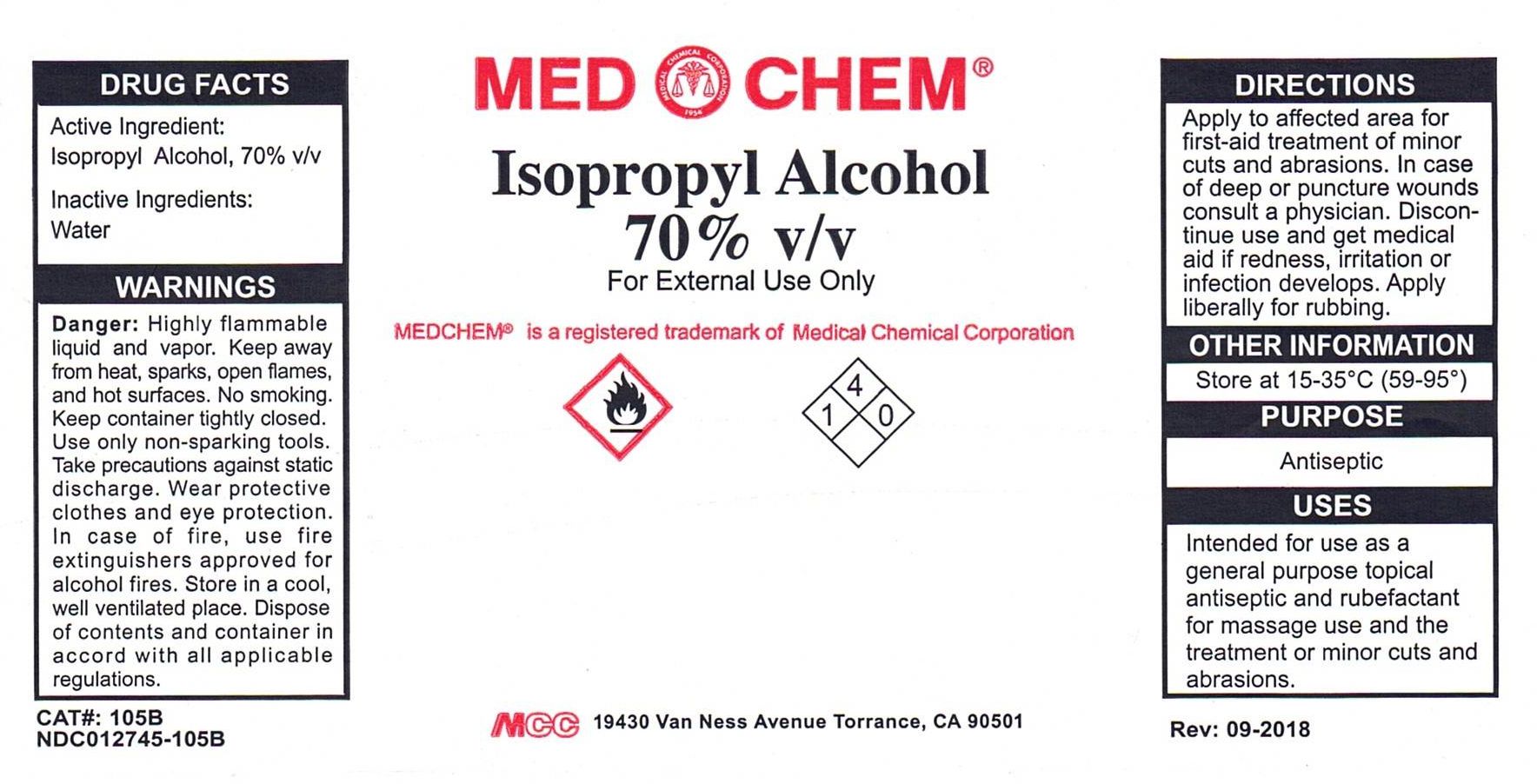 DRUG LABEL: Isopropyl Alcohol
NDC: 12745-105 | Form: LIQUID
Manufacturer: Medical Chemical Corporation
Category: otc | Type: HUMAN OTC DRUG LABEL
Date: 20250731

ACTIVE INGREDIENTS: ISOPROPYL ALCOHOL 70.14 g/100 mL
INACTIVE INGREDIENTS: WATER

ISOPROPYL ALCOHOL

PURPOSE

Antiseptic

INDICATIONS AND USAGE

Directions: Apply to affected area for first-aid treatment of minor cuts and abrasions. In case of deep or puncture wounds consult a physician. Discontinue use and get medical aid if redness, irritation or infection develops. Apply liberally for rubbing.

Active ingredient: Isopropyl alcohol, 70%

KEEP OUT OF REACH OF CHILDREN

Warnings: For external use only. Avoid contact with eyes or mucous membranes. Ingestion will result in gastrointestinal distress, unconsciousness and death. Keep out of reach of children. In case of ingestion contact a poison control center immediately.

USER SAFETY WARNINGS

Flammable: Avoid sources of ignition. Do not use around open flames.

WARNINGS

Warnings: For external use only. Avoid contact with eyes or mucous membranes. Ingestion will result in gastrointestinal distress, unconsciousness and death. Keep out of reach of children. In case of ingestion contact a poison control center immediately.

Inactive Ingredients: Water

DOSAGE AND ADMINISTRATION

Directions: Apply to affected area for first-aid treatment of minor cuts and abrasions. In case of deep or puncture wounds consult a physician. Discontinue use and get medical aid if redness, irritation or infection develops. Apply liberally for rubbing.

PACKAGE LABEL

ipa70label.jpg